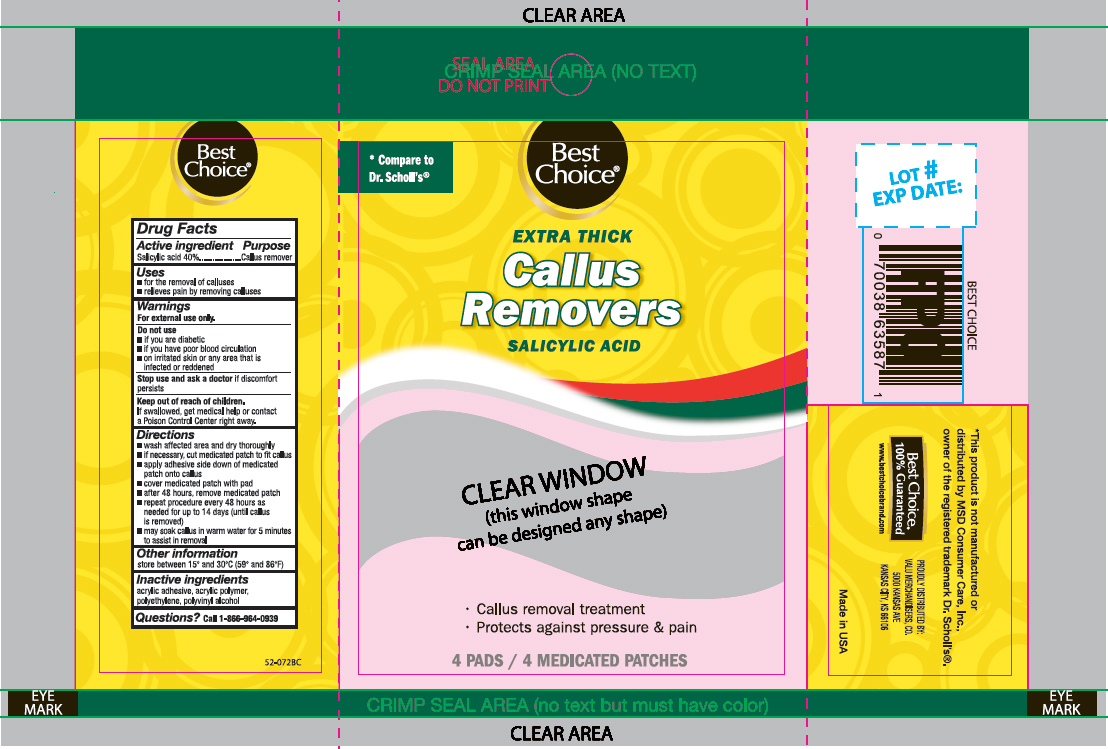 DRUG LABEL: Salicylic acid
NDC: 63941-551 | Form: PATCH
Manufacturer: VALU MERCHANDISERS, CO
Category: otc | Type: HUMAN OTC DRUG LABEL
Date: 20260115

ACTIVE INGREDIENTS: SALICYLIC ACID 40 mg/4 1
INACTIVE INGREDIENTS: POLYVINYL ALCOHOL; HIGH DENSITY POLYETHYLENE

Best Choice Medicated Extra Thick Callus Removers

Active ingredient

Salicylic acid 40%

Purpose

Callus remover

Use

- for the removal of calluses
- relieves pain by removing calluses

Warnings

For external use only.

Do not use

- if you are a diabetic
- if you have poor blood circulation
- on irritated skin, on any area that is infected or reddened

Stop use and ask a doctor

if discomfort persists

Keep out of reach of children.

If swallowed, get medical help or contact a Poison Control Center right away.

Directions

- wash affected area and dry area thoroughly
- if necessary, cut medicated patch to fit callus
- apply adhesive side down of medicated patch onto callus
- cover medicated patch with pad
- after 48 hours, remove medicated patch
- repeat procedure every 48 hours as needed for up to 14 days (until corn is removed)
- may soak corn in warm water for 5 minutes to assist in removal

Other information

store between 15°C to 30°C (59°F to 86°F)

Inactive ingredients

acrylic adhesive, acrylic polymer, polyethylene, polyvinyl alcohol

Questions?

call 1-866-964-0939

Principal Display Panel

Best Choice

EXTRA THICK
Callus Removers
Salicylic Acid

- Callus removal treatment
- Protects against pressure & pain

4 Pads/ 4 Medicated Patches